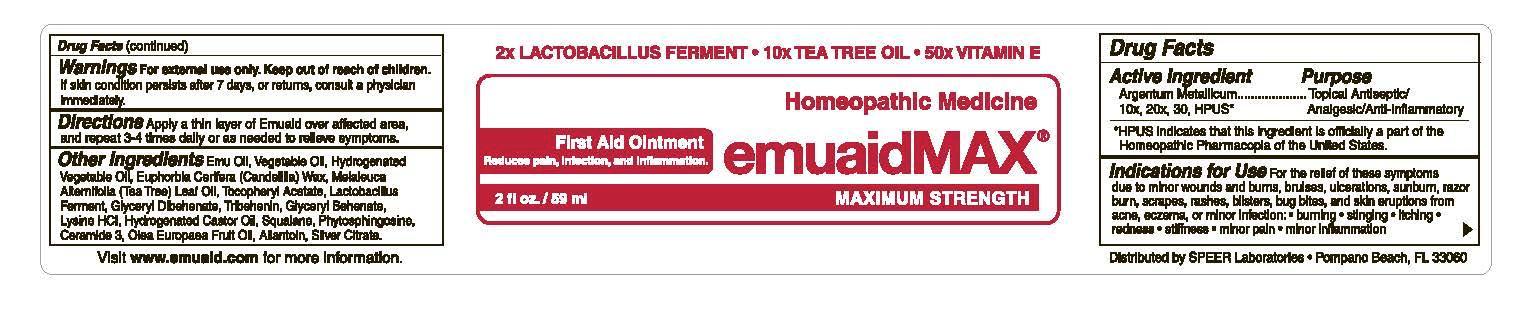 DRUG LABEL: emuaidMAX
NDC: 55926-0025 | Form: OINTMENT
Manufacturer: Speer Laboratories, LLC
Category: homeopathic | Type: HUMAN OTC DRUG LABEL
Date: 20241214

ACTIVE INGREDIENTS: SILVER 10 [hp_X]/100 mL
INACTIVE INGREDIENTS: EMU OIL; SOYBEAN OIL; PALM OIL; CANOLA OIL; CANDELILLA WAX; LACTOBACILLUS REUTERI; TRIBEHENIN; GLYCERYL DIBEHENATE; LYSINE HYDROCHLORIDE; HYDROGENATED CASTOR OIL; SQUALANE; TEA TREE OIL; .ALPHA.-TOCOPHEROL ACETATE; PHYTOSPHINGOSINE; CERAMIDE 3; OLIVE OIL; ALLANTOIN; SILVER CITRATE

Active Ingredient

10x, 20x, 30 HPUS*

* HPUS indicates that this ingredient is officially a part of the Homeopathic Pharmacopia of the United States

Purpose

Topical Antiseptic, Analgesic, Anti-Inflammatory

Indications for Use

For the relief of these symptoms due to minor wounds and burns, bruises, ulcerations, sunburn, razor burn, scrapes, rashes, blisters, bug bites, and skin eruptions from acne, eczema, or minor infection: • burning • stinging • itching • redness • stiffness • minor pain • minor inflammation

Warnings

For external use only. If skin condition persists after 7 days, or returns, consult a physician immediately.

Keep out of reach of children.

Directions

Apply a thin layer of Emuaid over affected area, and repeat 3-4 times daily or as needed to relieve symptoms.

Inactive Ingredients

Emu oil, Soybean Oil, Palm Oil, Canola Oil, Candelilla Wax, Lactobacillus Reuteri, Tribehenin, Glyceryl Behenate, Lysine Hydrochloride, Hydrogenated Castor Oil, Squalane, Tea Tree Oil, .Alpha.-Tocopherol Acetate, Phytosphingosine, Ceramide 3, Olive Oil, Allantoin, Silver Citrate

Distributed by Speer Laboratories, LLC, Pompano Beach, FL 33080

Visit www.emuaid.com for more information.

Homeopathic Medicine emuaidMAX®

2x Lactobacillus Ferment • 10x Tea Tree Oil • 50x Vitamin E

First Aid Ointment

Reduces pain, infection, and inflammation

MAXIMUM STRENGTH

2 fl. oz./ 59 mL